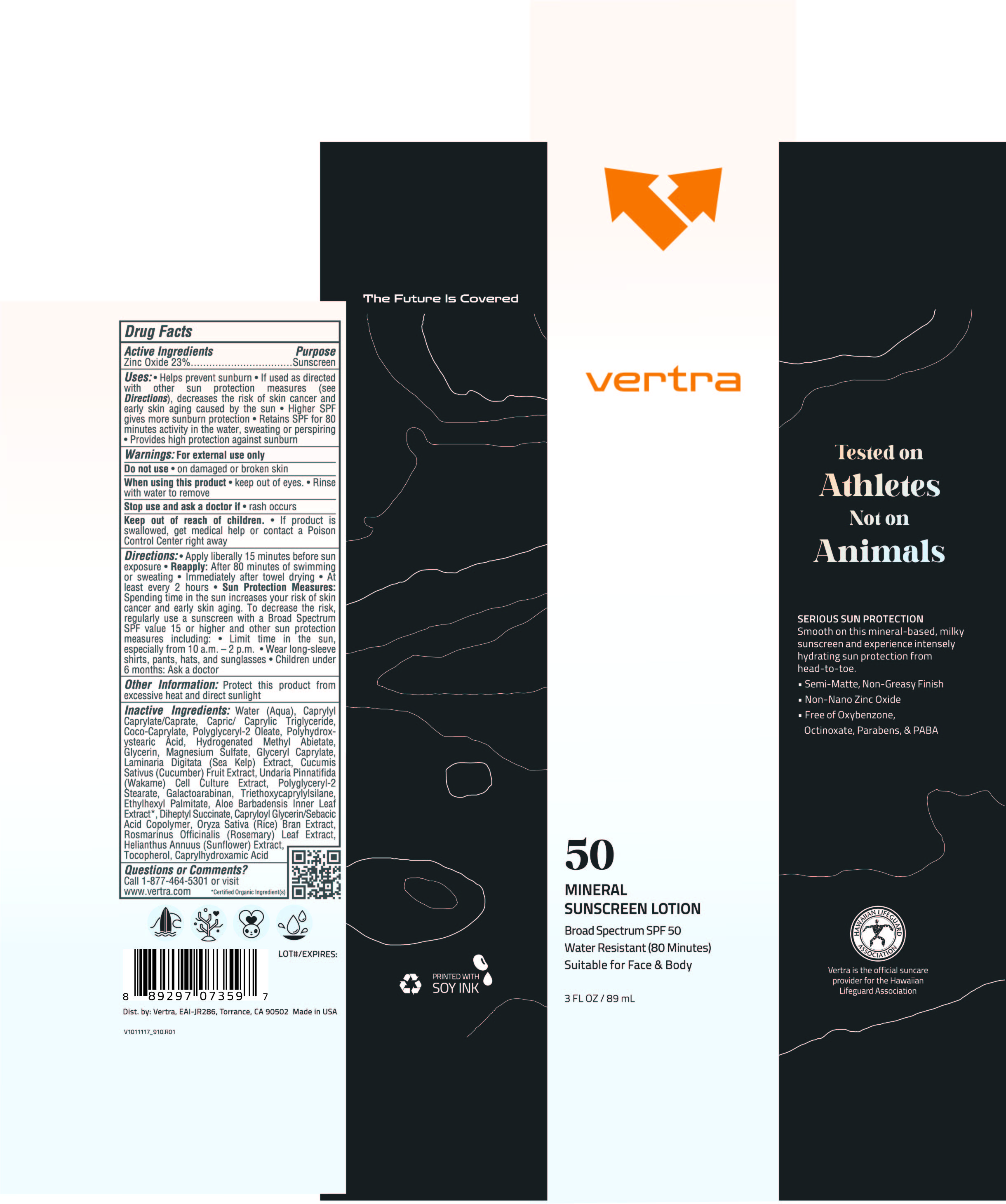 DRUG LABEL: Vertra Mineral Sunscreen Broad Spectrum SPF 50
NDC: 71014-042 | Form: LOTION
Manufacturer: Eai-jr 286, Inc
Category: otc | Type: HUMAN OTC DRUG LABEL
Date: 20250320

ACTIVE INGREDIENTS: ZINC OXIDE 23 g/100 mL
INACTIVE INGREDIENTS: WATER; CAPRYLYL CAPRYLATE/CAPRATE; MEDIUM-CHAIN TRIGLYCERIDES; CUCUMBER; CAPRYLOYL GLYCERIN/SEBACIC ACID COPOLYMER (2000 MPA.S); RICE BRAN; ROSEMARY; TOCOPHEROL; CAPRYLHYDROXAMIC ACID; LAMINARIA DIGITATA; POLYGLYCERYL-2 STEARATE; GLYCERIN; ALOE BARBADENSIS LEAF; ETHYLHEXYL PALMITATE; GALACTOARABINAN; POLYGLYCERYL-2 OLEATE; HELIANTHUS ANNUUS FLOWERING TOP; HYDROGENATED METHYL ABIETATE; COCO-CAPRYLATE; GLYCERYL CAPRYLATE; DIHEPTYL SUCCINATE; POLYHYDROXYSTEARIC ACID (2300 MW); TRIETHOXYCAPRYLYLSILANE; MAGNESIUM SULFATE; UNDARIA PINNATIFIDA

Vertra Mineral Sunscreen Lotion Broad Spectrum SPF 50

Active Ingredients Purpose

Zinc Oxide 23%.....Sunscreen

Uses

- Helps prevent sunburn
- If used as directed with other sun protection measures (see Directions), decreases the risk of skincancer and early skin aging caused by the sun

Keep out of reach of children.If product is swallowed, get medical help or contact a Poison Control Center Right away.

Stop use and ask a doctor if

- rash occurs

Warnings: For external use only

Do not use

- on damaged or broken skin

When using this product

- keep out of eyes
- Rinse with water to remove

Directions:

- Apply liberally 15 minutes before sun exposure

Reapply: After 80 minutes of swimming or sweating

- Immediately after towel drying
- At least every 2 hours

- Sun Protection Measures: Spending time in the sun increases your risk of skin cancer and early skin aging. To decrease this risk, regularly use a sunscreen with a Broad Spectrum SPF value of 15 or higher and other sun protection measures including:
- Limit time in the sun, especially from 10 a.m.- 2 p.m.
- Wear long-sleeved shirts, pants, hats and sunglasses
- Children under 6 months: Ask a doctor

INACTIVE INGREDIENT

Inactive ingredients: Water (Aqua), Caprylyl Caprylate/Caprate, Capric/ Caprylic Triglyceride, Coco-Caprylate, Polyglyceryl-2 Oleate, Polyhydroxystearic Oleate, Polyhydroxystearic Acid, Hydrogenated Methyl Abietate, Glycerin, Magnesium Sulfate, Glyceryl Caprylate, Laminaria Digitata (Sea Kelp) Extract, Cucumis Sativus (Cucumber) Fruit Extract, Undaria Pinnatifida (Wakame) Cell Culture Extract, Polyglyceryl-2 Stearate, Galactoarabinan, Triethoxycaprylylsilane, Ethylhexyl Palmitate, Aloe Barbadensis Innter Leaf Extract, Diheptyl Succinate, Capryloyl Glycerin/Sebacic Acid Copolymer, Oryza Sativa (Rice) Bran Extract, Rosmarinus Officinalis (Rosemary) Leaf Extract, Helianthus Annuus (Sunflower) Extract, Tocopherol, Caprylhydroxamic Acid

PACKAGE LABEL

vertra

50

Mineral

Sunscreen Lotion

Broad Spectrum SPF 50

Water Resistant (80 Minutes)

Suitable for Face & Body

3 FL OZ / 89 mL